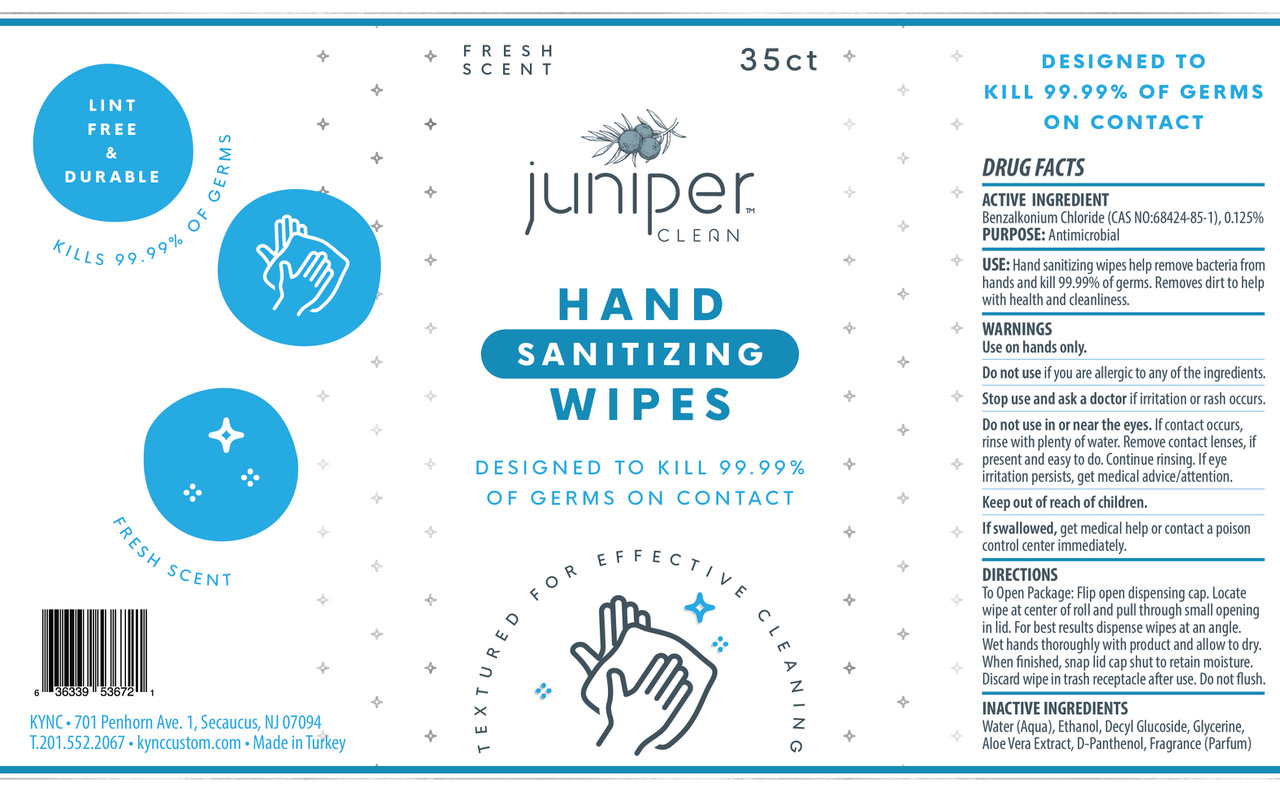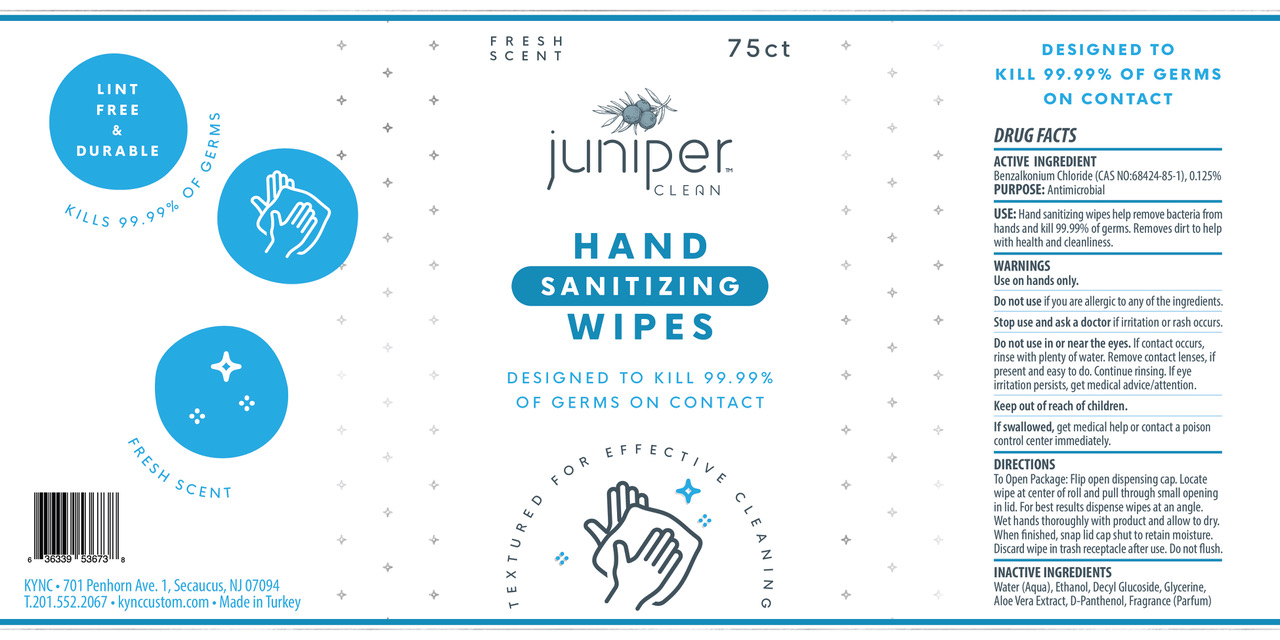 DRUG LABEL: Hand Sanitizer Wipes
NDC: 76557-001 | Form: CLOTH
Manufacturer: KYNC Design LLC
Category: otc | Type: HUMAN OTC DRUG LABEL
Date: 20260123

ACTIVE INGREDIENTS: BENZALKONIUM CHLORIDE 0.125 mg/100 mg
INACTIVE INGREDIENTS: CLOVE; DECYL GLUCOSIDE; DEXPANTHENOL; ALOE VERA LEAF; GLYCERIN; WATER; ALCOHOL

Hand Sanitizer Wipes

SPL UNCLASSIFIED SECTION

Active Ingredient(s)

Benzalkonium Chloride (CAS NO: 68424-85-1), 0.125% .

Purpose

Antimicrobial

Use

Hand sanitizing wipes help remove bacteria from hands and kill 99.99% of germs. Removes dirt to help with health and cleanliness.

WARNINGS

Use on hands only.

Do not use

If you are allergic to any of the ingredients.

Stop use and ask a doctor

if irritation or rash occurs.

Do not use in or near the eyes.

If contact occurs rinse with plenty of water. Remove contact lenses, if present and easy to do. Continue rinsing. If eye irritation persists, get medical advice/attention.

Keep out of reach of children.

If swallowed, get medical help or contact a poison control center immediately.

Directions

To Open Package: Flip open dispensing cap. Locate wipe at center of roll and pull through small openning in lid. For best results dispense wipes at an angle. Wet hands thoroughly with product and allow to dry. When finished, snap lid cap shut to retain moisture. Discard wipe in trash receptacle after use. Do not flush.

Inactive ingredients

Water(Aqua), Ethanol, Decyl Glucoside, Glycerine, Aloe Vera Extract, D-Panthenol, Fragrance (Perfume)

Package Label - Principal Display Panel

110 mL NDC: 76557-001-01

245 mL NDC: 76557-001-01